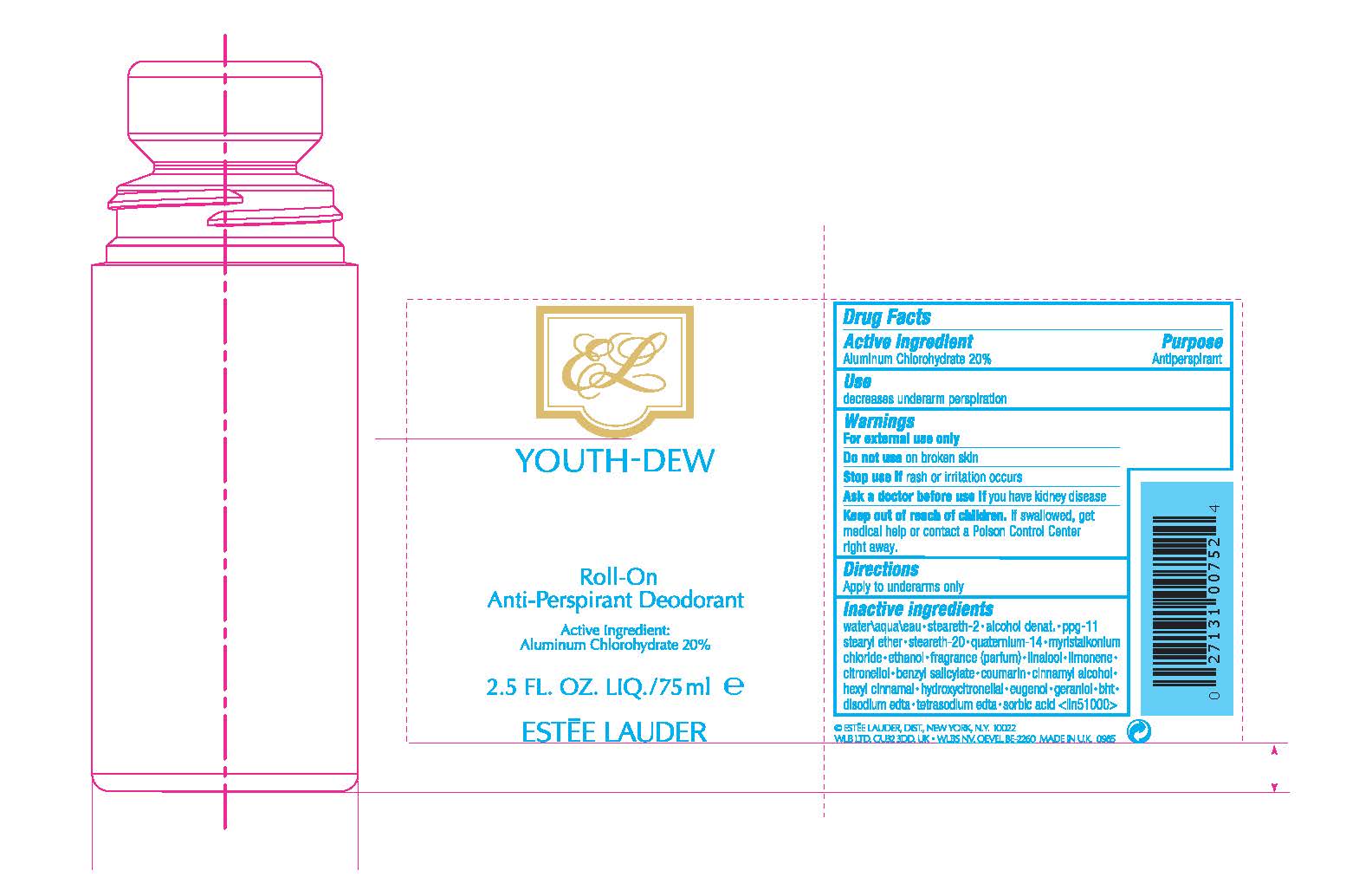 DRUG LABEL: YOUTH DEW ROLL-ON ANTIPERSPIRANT DEODORANT
NDC: 11559-001 | Form: LIQUID
Manufacturer: ESTEE LAUDER INC
Category: otc | Type: HUMAN OTC DRUG LABEL
Date: 20240712

ACTIVE INGREDIENTS: ALUMINUM CHLOROHYDRATE 200 mg/1 mL
INACTIVE INGREDIENTS: LINALOOL, (+)-; HYDROXYCITRONELLAL; GERANIOL; CITRONELLOL ACETATE, (R)-; EUGENOL; LIMONENE, (+)-; CINNAMYL ALCOHOL; COUMARIN; .ALPHA.-HEXYLCINNAMALDEHYDE; EDETATE TRISODIUM; SORBIC ACID; WATER; STEARETH-2; ALCOHOL; POLYPROPYLENE GLYCOL 11 STEARYL ETHER; STEARETH-20; FRAGRANCE LAVENDER & CHIA F-153480; MYRISTALKONIUM CHLORIDE; QUATERNIUM-14; BENZYL SALICYLATE

YOUTH DEW ROLL-ON ANTIPERSPIRANT DEODORANT

ACTIVE INGREDIENT

ACTIVE INGREDIENT: ALUMINUM CHLOROHYDRATE 20.00%

INDICATIONS AND USAGE

USES: DECREASES UNDERARM PERSPIRATION

WARNINGS:

- FOR EXTERNAL USE ONLY
- DO NOT USE ON BROKEN SKIN
- STOP USE IF RASH OR IRRITATION OCCURS
- ASK A DOCTOR BEFORE USE IF YOU HAVE KIDNEY DISEASE

KEEP OUT OF REACH OF CHILDREN. IF SWALLOWED, GET MEDICAL HELP OR CONTACT A POISON CONTROL CENTER RIGHT AWAY.

DOSAGE AND ADMINISTRATION

DIRECTIONS: APPLY TO UNDERARMS ONLY

Inactive ingredients

water\aqua\eau•steareth-2•alcohol denat.•ppg-11 stearyl ether•steareth-20•youth-dew fragrance (parfum)•myristalkonium chloride•quaternium-14•benzyl salicylate•linalool•hydroxycitronellal•geraniol•citronellol•eugenol•limonene•cinnamyl alcohol•coumarin•hexyl cinnamal•trisodium edta•sorbic acid <iln37908>

PRINCIPAL DISPLAY PANEL - 75 ml Bottle Label

YOUTH-DEW

Roll-On
Anti-Perspirant Deodorant

Active Ingredient:
Aluminum Chlorohydrate 20%

2.5 FL. OZ. LIQ. /75ml ℮

ESTĒE LAUDER